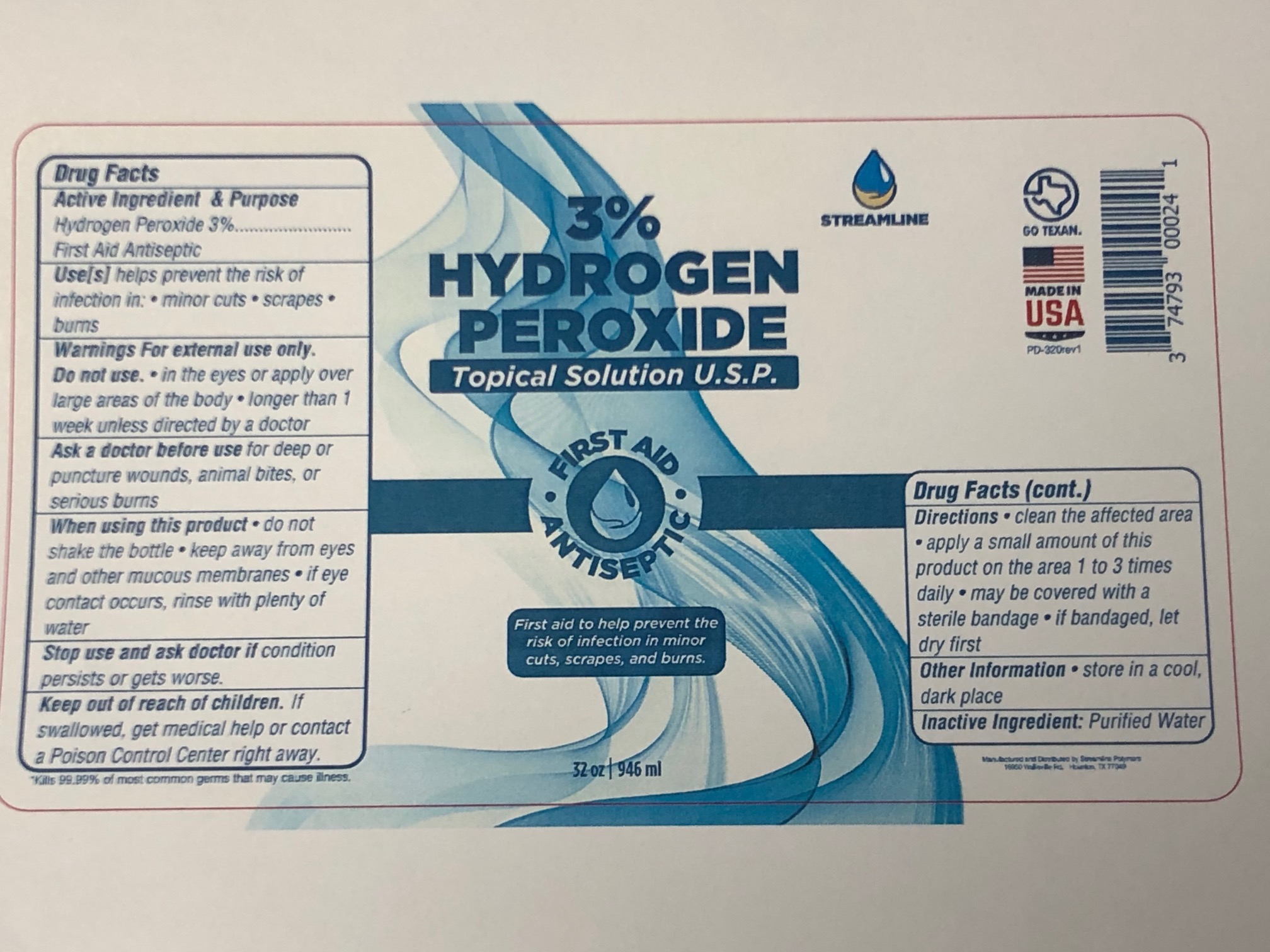 DRUG LABEL: 3% Hydrogen Peroxide
NDC: 74793-0011 | Form: LIQUID
Manufacturer: Streamline Polymers LLC
Category: otc | Type: HUMAN OTC DRUG LABEL
Date: 20220113

ACTIVE INGREDIENTS: HYDROGEN PEROXIDE 3 mL/100 mL
INACTIVE INGREDIENTS: WATER

Hydrogen Peroxide 3%

Hydrogen Peroxide 3%

This is a solution of 3% hydrogen peroxide and purified water.

Active Ingredient(s)

3%Hydrogen Peroxide

Purpose

First Aid Antiseptic

Use

helps prevent the risk of infection in minor cuts, scrapes, burns

Warnings

Do not use in the eyes or apply over large areas of the body. Do not use longer than 1 week unless directed by a doctor.

Do not use

- in eyes or apply over large areas of the body
- longer than 1 week unless directed by a doctor

When using this product do not shake the bottle; keep away from eyes and other mucous membranes; if eye contact occurs, rinse with plenty of water.

Stop use and ask a doctor if condition persists or gets worse.

Keep out of reach of children. If swallowed, get medical help or contact a Poison Control Center right away.

Directions

- Clean the affected area
- apply a small amount of this product on the area 1 to 3 times daily
- may be covered with a sterile bandage
- if bandaged, let dry first.

Other information

- Store in a cool, dark place.

Inactive ingredients

purified water USP